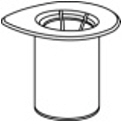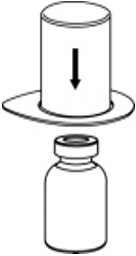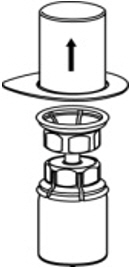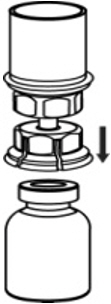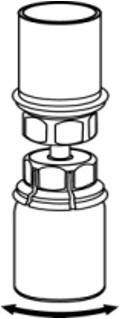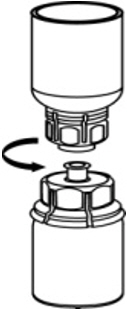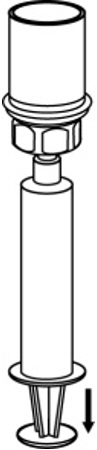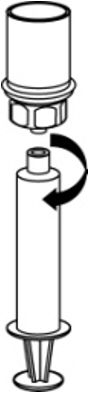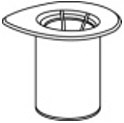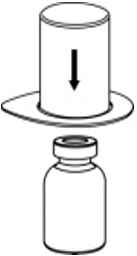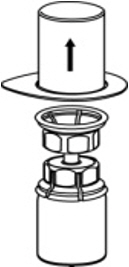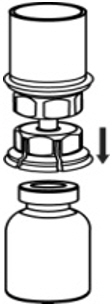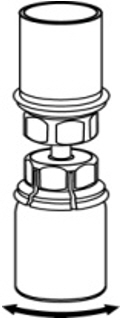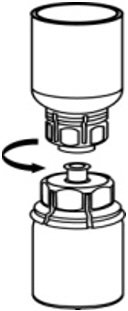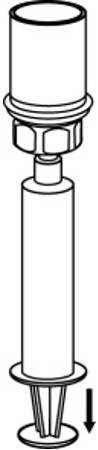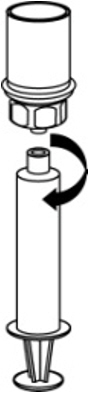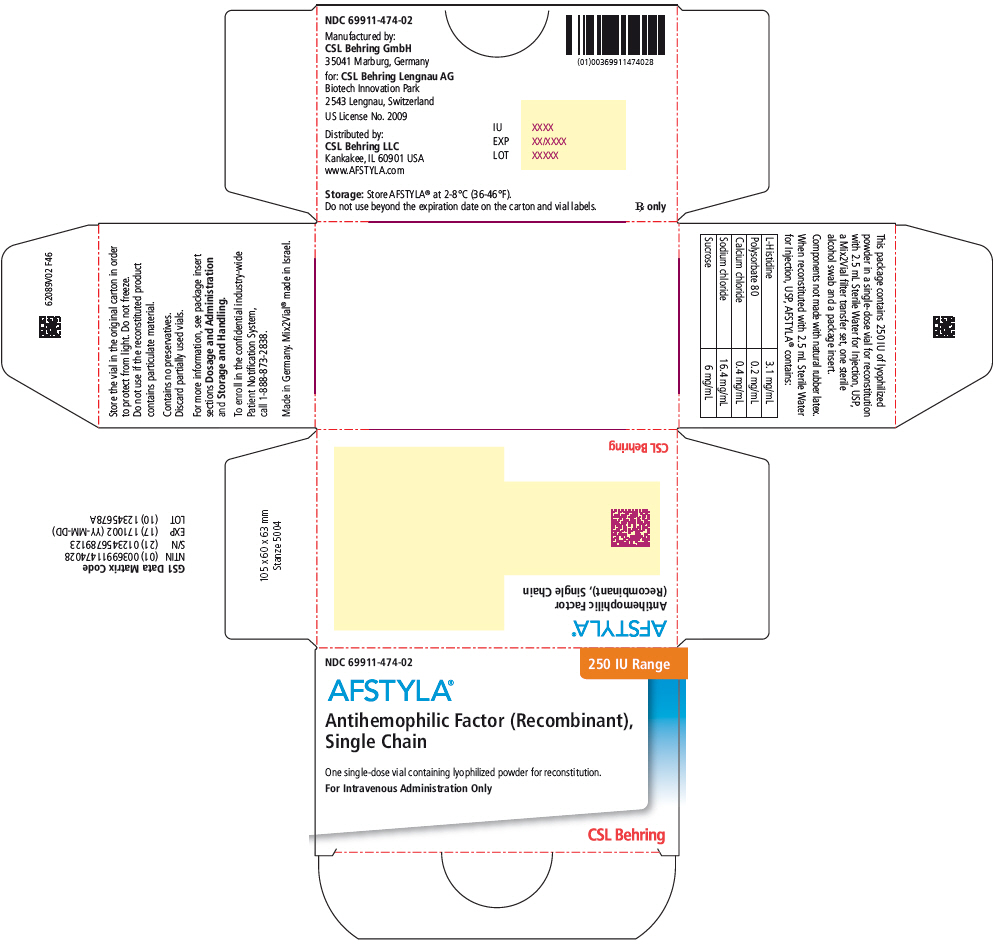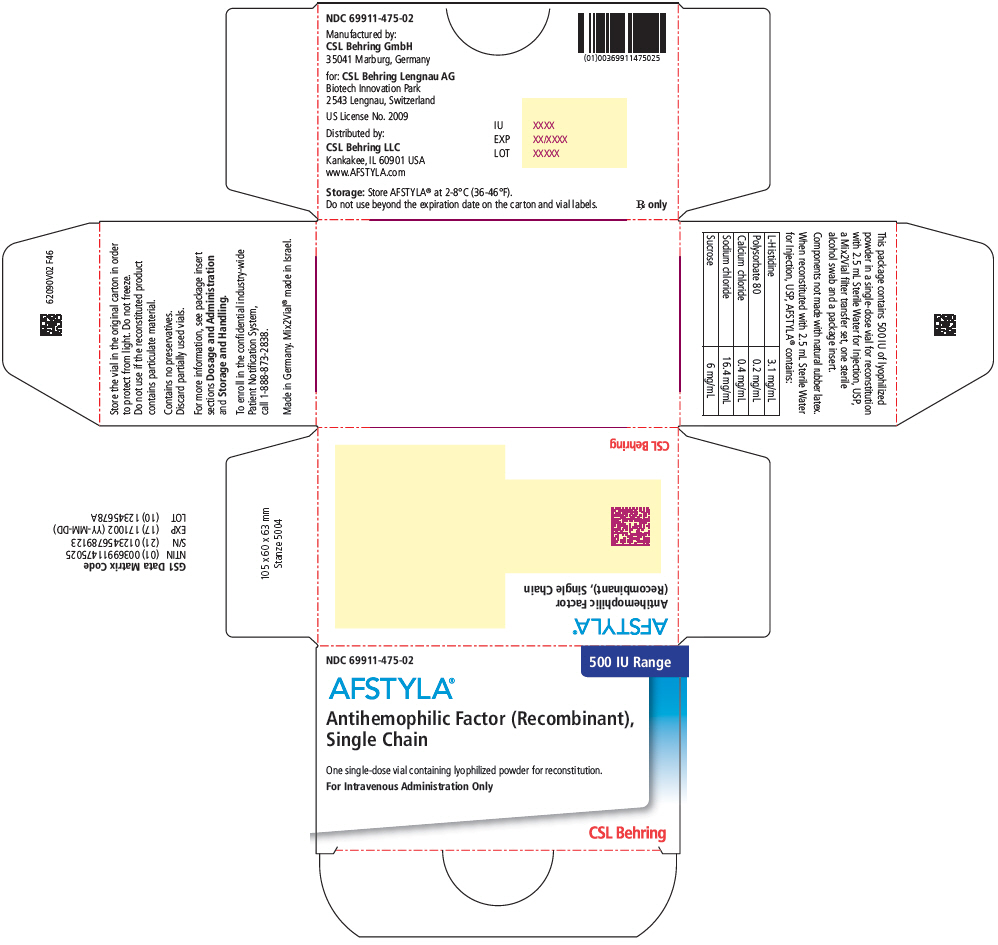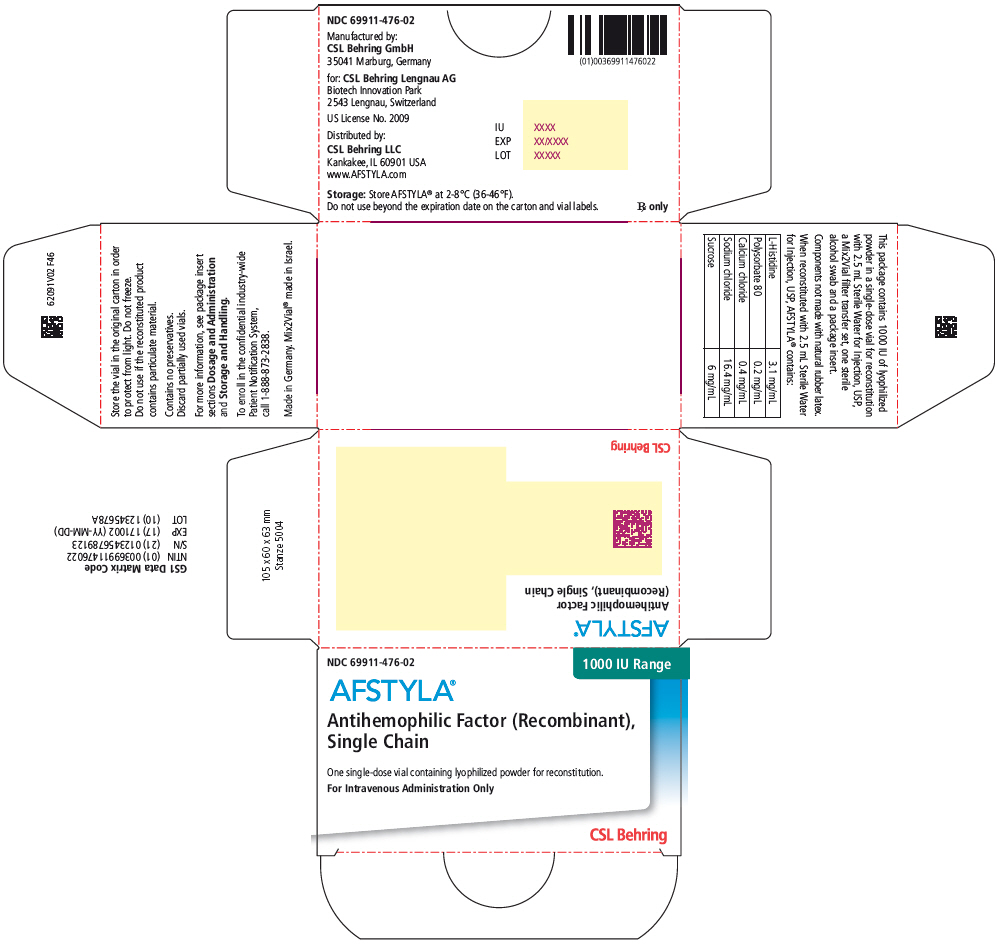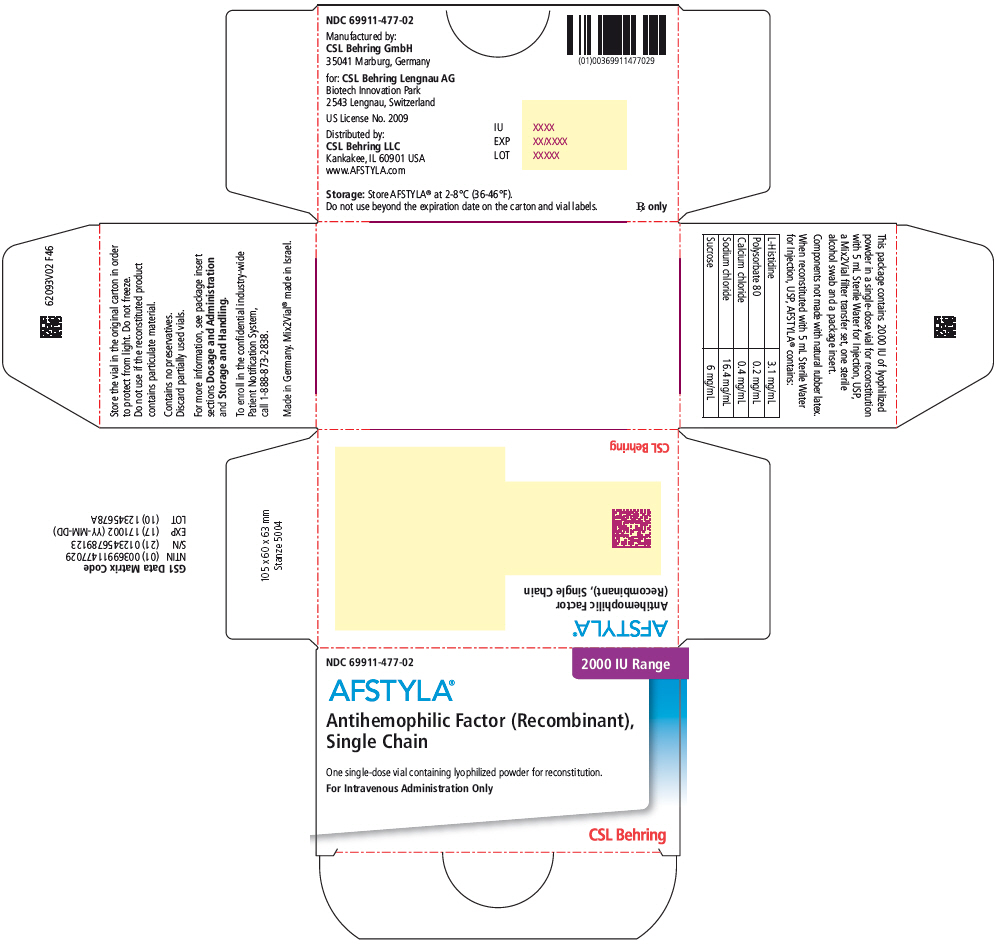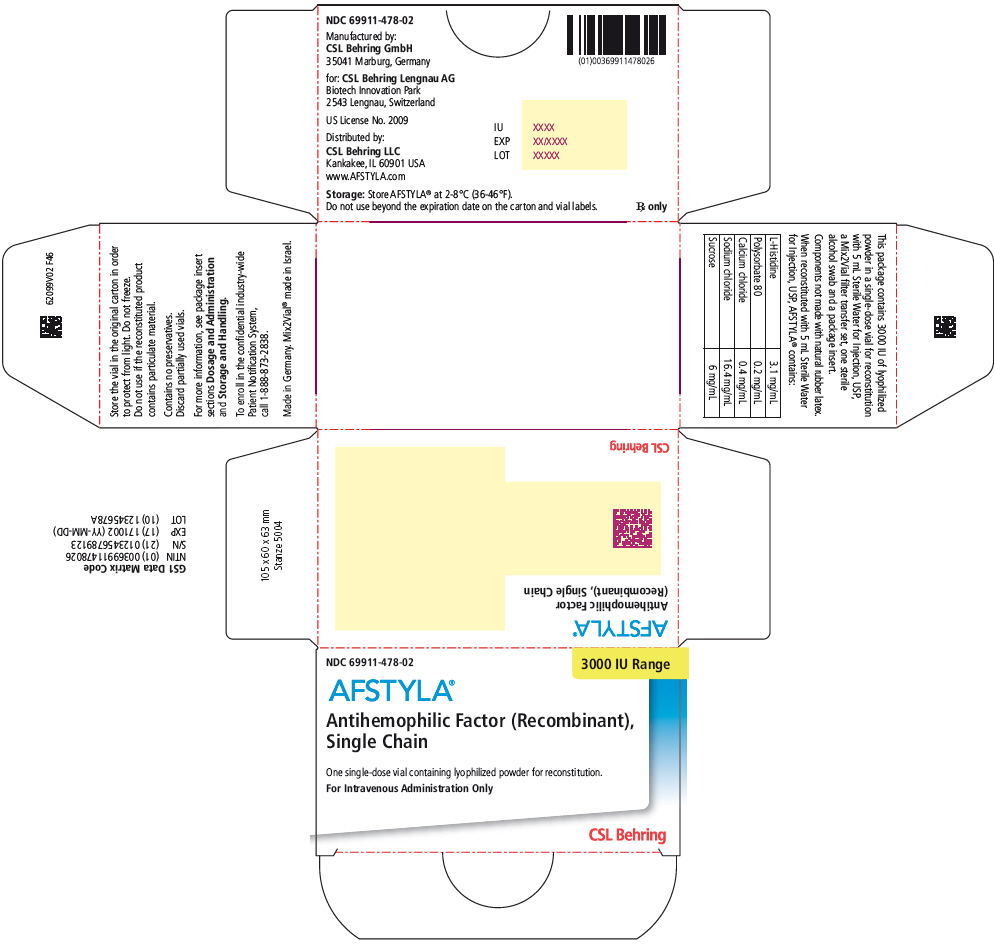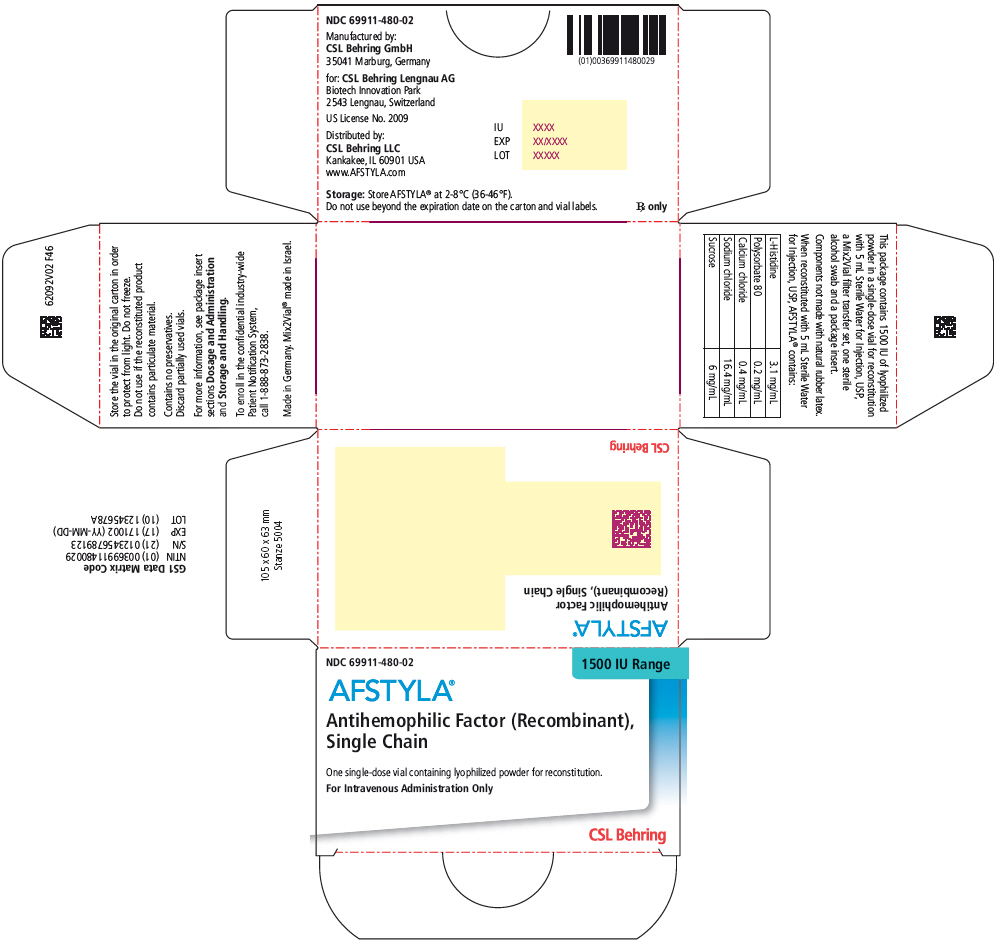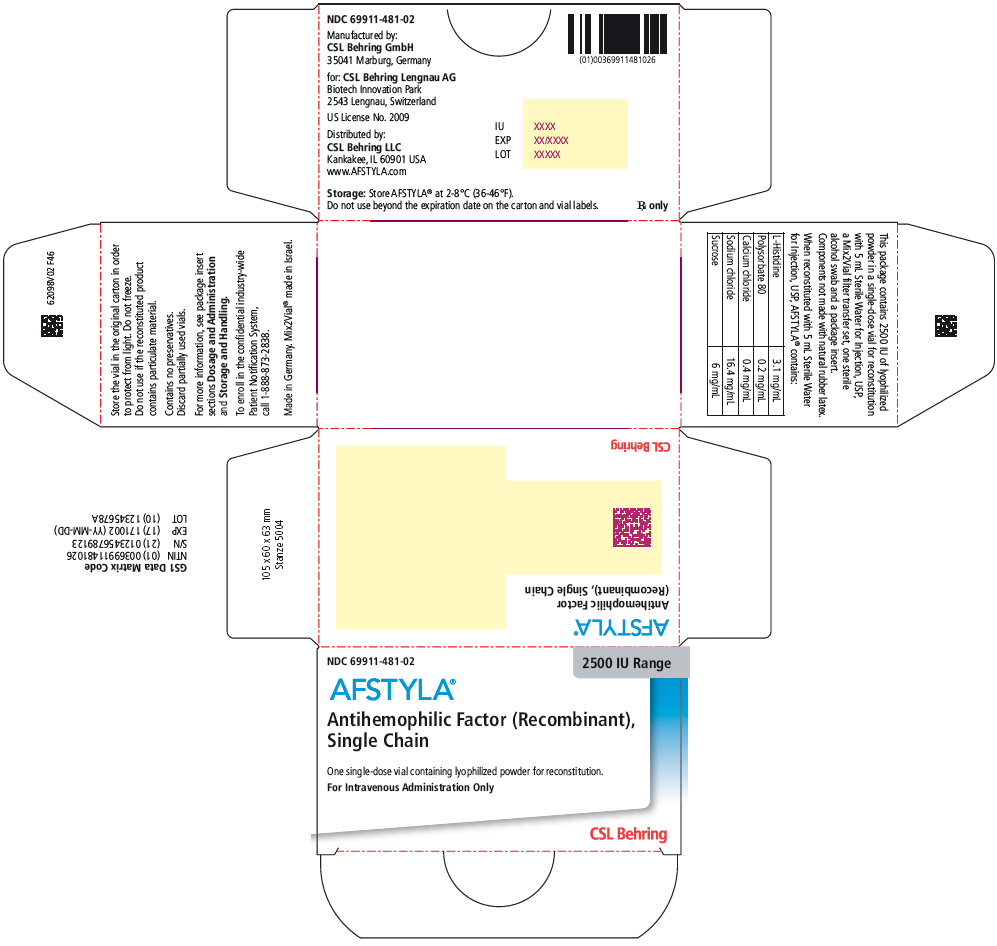 DRUG LABEL: AFSTYLA 
NDC: 69911-474 | Form: KIT | Route: INTRAVENOUS
Manufacturer: CSL Behring Lengnau AG
Category: other | Type: PLASMA DERIVATIVE
Date: 20230623

ACTIVE INGREDIENTS: LONOCTOCOG ALFA 250 [iU]/2.5 mL
INACTIVE INGREDIENTS: Histidine; Polysorbate 80; Calcium chloride; Sodium chloride; Sucrose; water

HIGHLIGHTS OF PRESCRIBING INFORMATION

These highlights do not include all the information needed to use AFSTYLA safely and effectively. See full prescribing information for AFSTYLA.
AFSTYLA® [Antihemophilic Factor (Recombinant), Single Chain]
Lyophilized Powder for Solution for Intravenous Injection
Initial U.S. Approval: 2016

1 INDICATIONS AND USAGE

AFSTYLA, Antihemophilic Factor (Recombinant), Single Chain, is a recombinant, antihemophilic factor indicated in adults and children with hemophilia A (congenital Factor VIII deficiency) for:

- On-demand treatment and control of bleeding episodes,
- Routine prophylaxis to reduce the frequency of bleeding episodes,
- Perioperative management of bleeding.

Limitation of Use

AFSTYLA is not indicated for the treatment of von Willebrand disease (1).

2 DOSAGE AND ADMINISTRATION

For intravenous use after reconstitution only.

- Each vial of AFSTYLA is labeled with the amount of recombinant Factor VIII in international units (IU or unit). One unit per kilogram body weight will raise the Factor VIII level by 2 IU/dL. (2.1)
- Plasma Factor VIII levels can be monitored using either a chromogenic assay or a one-stage clotting assay – routinely used in US clinical laboratories. If the one-stage clotting assay is used, multiply the result by a conversion factor of 2 to determine the patient's Factor VIII activity level. (2.1, 5.3)

Calculating Required Dose: (2.1)

Dose (IU) = Body Weight (kg) × Desired Factor VIII Rise (IU/dL or % of normal) × 0.5 (IU/kg per IU/dL)

Routine Prophylaxis: (2.1)

- Adults and adolescents (≥12 years): The recommended starting regimen is 20 to 50 IU per kg of AFSTYLA administered 2 to 3 times weekly.
- Children (<12 years): The recommended starting regimen is 30 to 50 IU per kg of AFSTYLA administered 2 to 3 times weekly. More frequent or higher doses may be required in children <12 years of age to account for the higher clearance in this age group.
- The regimen may be adjusted based on patient response.

Perioperative Management: (2.1)

Ensure the appropriate Factor VIII activity level is achieved and maintained.

3 DOSAGE FORMS AND STRENGTHS

AFSTYLA is available as a white or slightly yellow lyophilized powder supplied in single-dose vials containing nominally 250, 500, 1000, 1500, 2000, 2500, or 3000 International Units (IU). (3)

4 CONTRAINDICATIONS

Do not use in patients who have had life-threatening hypersensitivity reactions, including anaphylaxis to AFSTYLA or its excipients, or hamster proteins. (4)

5 WARNINGS AND PRECAUTIONS

- Hypersensitivity reactions, including anaphylaxis, are possible. Should symptoms occur, immediately discontinue AFSTYLA and administer appropriate treatment. (5.1)
- Formation of neutralizing antibodies (inhibitors) to Factor VIII has been reported following administration of AFSTYLA; previously untreated patients (PUPs) are at greater risk.. If expected plasma Factor VIII activity levels are not attained, or if bleeding is not controlled with an appropriate dose, perform an assay that measures Factor VIII inhibitor concentration. (5.2)
- If the one-stage clotting assay is used, multiply the result by a conversion factor of 2 to determine the patient's Factor VIII activity level. (5.3)

6 ADVERSE REACTIONS

- The most common adverse reactions reported in clinical trials (>0.5% of subjects) were Factor VIII inhibition in previously untreated patients (PUPs), dizziness and hypersensitivity. (6)

To report SUSPECTED ADVERSE REACTIONS, contact the CSL Behring Pharmacovigilance Department at 1-866-915-6958 or FDA at 1-800-FDA-1088 or www.fda.gov/medwatch.

8 USE IN SPECIFIC POPULATIONS

- Pediatric: Clearance (based on per kg body weight) is higher in pediatric patients 0 to <12 years of age. Higher and/or more frequent dosing may be needed. (8.4)

FULL PRESCRIBING INFORMATION

1 INDICATIONS AND USAGE

AFSTYLA, Antihemophilic Factor (Recombinant), Single Chain is a recombinant, antihemophilic factor indicated in adults and children with hemophilia A (congenital Factor VIII deficiency) for:

- On-demand treatment and control of bleeding episodes,
- Routine prophylaxis to reduce the frequency of bleeding episodes,
- Perioperative management of bleeding.

Limitation of Use

AFSTYLA is not indicated for the treatment of von Willebrand disease.

2 DOSAGE AND ADMINISTRATION

For intravenous use after reconstitution only.

2.1 Dosing Guidelines

- Dose and duration of treatment depend on the severity of the Factor VIII deficiency, the location and extent of bleeding, and the patient's clinical condition.
- Each vial of AFSTYLA states the actual amount of Factor VIII activity in International Units (IU) as determined by chromogenic assay. One IU corresponds to the activity of Factor VIII contained in 1 milliliter (mL) of normal human plasma.
- Plasma Factor VIII levels can be monitored using either a chromogenic assay or a one-stage clotting assay – routinely used in US clinical laboratories. If the one-stage clotting assay is used, multiply the result by a conversion factor of 2 to determine the patient's Factor VIII activity level [see Warnings and Precautions (5.3)].

Calculating Required Dose

- The calculation of the required dose of Factor VIII is based on the empirical finding that 1 IU Factor VIII per kg body weight raises the plasma Factor VIII level by 2 IU/dL.
  The expected in vivo peak increase in Factor VIII level expressed as IU/dL (or % of normal) is estimated using the following formula:
  Estimated Increment of Factor VIII (IU/dL or % of normal) = [Total Dose (IU)/body weight (kg)] × 2 (IU/dL per IU/kg)
  The dose to achieve a desired in vivo peak increase in Factor VIII level may be calculated using the following formula:
  Dose (IU) = body weight (kg) × Desired Factor VIII rise (IU/dL or % of normal) × 0.5 (IU/kg per IU/dL)
- The amount of AFSTYLA to be administered and the frequency of administration should always be oriented to the clinical effectiveness in the individual case.

On-demand Treatment and Control of Bleeding Episodes

A guide for dosing AFSTYLA in the treatment and control of bleeding episodes is provided in Table 1. Consideration should be given to maintaining a Factor VIII activity at or above the target range.

Table 1. Dosing for On-demand Treatment and Control of Bleeding Episodes
Type of Bleeding Episode | Factor VIII Activity Level Required (% or IU/dL) | Frequency of Doses (hours)
Minor Uncomplicated hemarthrosis, minor muscle bleeding or oral bleeding | 20-40 | Repeat injection every 12-24 hours until the bleeding is resolved.
Moderate Muscle bleeding (except iliopsoas), hemarthrosis, or mild trauma | 30-60 | Repeat injection every 12-24 hours until the bleeding is resolved.
Major/Life-threatening Limb threatening hemorrhage, deep muscle bleeding (including iliopsoas), intracranial and retropharyngeal bleeding, fractures or head trauma | 60-100 | Repeat injection every 8-24 hours until bleed is resolved.

Routine Prophylaxis

- Adults and adolescents (≥12 years): The recommended starting regimen is 20 to 50 IU per kg of AFSTYLA administered 2 to 3 times weekly.
- Children (<12 years): The recommended starting regimen is 30 to 50 IU per kg of AFSTYLA administered 2 to 3 times weekly. More frequent or higher doses may be required in children <12 years of age to account for the higher clearance in this age group [see Clinical Pharmacology (12.3)].
- The regimen may be adjusted based on patient response.

Perioperative Management of Bleeding

A guide for dosing AFSTYLA during surgery (perioperative management of bleeding) is provided in Table 2. Consideration should be given to maintaining a Factor VIII activity at or above the target range.

Table 2. Target Factor VIII Activity Levels for Perioperative Management of Bleeding
Type of Surgery | Factor VIII Activity Level Required (% or IU/dL) | Frequency of Doses (hours) / Duration of Therapy (days)
Minor (including tooth extraction) | 30-60 | Repeat injection every 24 hours for at least 1 day, until healing is achieved.
Major (intracranial, intra-abdominal, intrathoracic, or joint-replacement) | 80-100 | Repeat injection every 8-24 hours until adequate wound healing, then continue therapy for at least another 7 days to maintain a Factor VIII activity of 30-60% (IU/dL).

2.2 Preparation and Reconstitution

- Reconstitute AFSTYLA using aseptic technique with diluent provided in the kit.
- Visually inspect the reconstituted solution for particulate matter prior to administration. The solution should be free from visible particles. Do not use if particulate matter is observed.

The procedures provided below are general guidelines for the preparation and reconstitution of AFSTYLA.

AFSTYLA Reconstitution Instructions

1. Ensure that the AFSTYLA vial and diluent vial are at room temperature. Prepare and administer using aseptic technique.
2. Place the AFSTYLA vial, diluent vial, and Mix2Vial® transfer set on a flat surface.
3. Remove AFSTYLA and diluent vial flip caps. Wipe the stoppers with the sterile alcohol swab provided and allow the stoppers to dry prior to opening the Mix2Vial transfer set package.
4. Open the Mix2Vial transfer set package by peeling away the lid (Fig. 1). Leave the Mix2Vial transfer set in the clear package.
  Fig. 1
5. Place the diluent vial on a flat surface and hold the vial tightly. Grip the Mix2Vial transfer set together with the clear package and push the plastic spike at the blue end of the Mix2Vial transfer set firmly through the center of the stopper of the diluent vial (Fig. 2).
  Fig. 2
6. Carefully remove the clear package from the Mix2Vial transfer set. Make sure that you pull up only the clear package, not the Mix2Vial transfer set (Fig. 3).
  Fig. 3
7. With the AFSTYLA vial placed firmly on a flat surface, invert the diluent vial with the Mix2Vial transfer set attached and push the plastic spike of the transparent adapter firmly through the center of the stopper of the AFSTYLA vial (Fig. 4). The diluent will automatically transfer into the AFSTYLA vial.
  Fig. 4
8. With the diluent and AFSTYLA vial still attached to the Mix2Vial transfer set, gently swirl the AFSTYLA vial to ensure that the AFSTYLA is fully dissolved (Fig. 5). Do not shake the vial.
  Fig. 5
9. With one hand, grasp the AFSTYLA side of the Mix2Vial transfer set and with the other hand grasp the blue diluent-side of the Mix2Vial transfer set, and unscrew the set into two pieces. (Fig. 6).
  Fig. 6
10. Draw air into an empty, sterile syringe. While the AFSTYLA vial is upright, screw the syringe to the Mix2Vial transfer set. Inject air into the AFSTYLA vial. While keeping the syringe plunger pressed, invert the system upside down and draw the concentrate into the syringe by pulling the plunger back slowly. (Fig. 7).
  Fig. 7
11. Now that the concentrate has been transferred into the syringe, firmly grasp the barrel of the syringe (keeping the plunger facing down) and unscrew the syringe from the Mix2Vial transfer set (Fig. 8).
  Fig. 8
12. After reconstitution, infuse immediately or within 4 hours. Reconstituted AFSTYLA may be stored at room temperature, not to exceed 25°C (77°F), for up to 4 hours. Do not freeze. Protect from direct sunlight.
13. Record treatment – Remove the peel-off portion of the label from each vial used, and affix it to the patient's treatment diary/log book or scan the vial if recording the infusion electronically.
14. If the dose requires more than one vial, use a separate, unused Mix2Vial® transfer set for each product vial. Repeat step 10 to pool the contents of the vial into one syringe.

2.3 Administration

- Use aseptic technique when administering AFSTYLA.
- Do not mix AFSTYLA with other medicinal products.
- Administer by intravenous injection. The rate of administration should be determined by the patient's comfort level. Do not exceed infusion rate of 10 mL per minute.
- Administer AFSTYLA at room temperature within 4 hours after reconstitution.
- AFSTYLA is for single-dose only. Following administration, discard any unused solution and all administration equipment in an appropriate manner as per local requirements.
- If a central venous access device (CVAD) is required, risk of CVAD-related complications including local infections, bacteremia and catheter site thrombosis should be considered.

3 DOSAGE FORMS AND STRENGTHS

AFSTYLA is available as a white or slightly yellow lyophilized powder supplied in single-dose vials containing nominally 250, 500, 1000, 1500, 2000, 2500, or 3000 IU. The actual potency is labeled on each AFSTYLA vial and carton.

4 CONTRAINDICATIONS

AFSTYLA is contraindicated in patients who have had life-threatening hypersensitivity reactions, including anaphylaxis to AFSTYLA or its excipients (e.g., polysorbate 80) [see Description (11)], or hamster proteins [see Warnings and Precautions (5.1)].

5 WARNINGS AND PRECAUTIONS

5.1 Hypersensitivity Reactions

Allergic-type hypersensitivity reactions, including anaphylaxis, are possible with AFSTYLA. Inform patients of the early signs of hypersensitivity reactions that may progress to anaphylaxis (including hives, generalized urticaria, tightness of the chest, wheezing, hypotension and pruritus). Immediately discontinue administration and initiate appropriate treatment if hypersensitivity reactions occur.

For patients with previous hypersensitivity reactions, consider premedication with antihistamines.

5.2 Neutralizing Antibodies

Formation of neutralizing antibodies (inhibitors) to Factor VIII has been reported following administration of AFSTYLA; previously untreated patients (PUPs) are at greatest risk [see Adverse Reactions (6.2)]. Monitor patients for the development of neutralizing antibodies (inhibitors) by appropriate clinical observations and laboratory tests. If expected plasma Factor VIII activity levels are not attained, or if bleeding is not controlled after AFSTYLA administration, the presence of an inhibitor (neutralizing antibody) should be suspected [see Warnings and Precautions (5.3)].

Contact a specialized hemophilia treatment center if a patient develops an inhibitor.

5.3 Monitoring Laboratory Tests

- Monitor plasma Factor VIII activity in patients receiving AFSTYLA using either the chromogenic assay or the one-stage clotting assay, which is routinely used in US clinical laboratories. The chromogenic assay result most accurately reflects the clinical hemostatic potential of AFSTYLA and is preferred. The one-stage clotting assay result underestimates the Factor VIII activity level compared to the chromogenic assay result by approximately one-half. If the one-stage clotting assay is used, multiply the result by a conversion factor of 2 to determine the patient's Factor VIII activity level. Incorrect interpretation of the Factor VIII activity obtained by the one-stage clotting assay could lead to unnecessary additional dosing, higher chronic dosing, or investigations for an inhibitor.
- Monitor for the development of Factor VIII inhibitors. Perform a Bethesda inhibitor assay if expected plasma Factor VIII activity levels are not attained or if bleeding is not controlled with the expected dose of AFSTYLA. Use Bethesda Units (BU) to report inhibitor levels.

6 ADVERSE REACTIONS

The most common adverse reactions (>0.5% of subjects) reported in clinical trials were Factor VIII inhibition in previously untreated patients (PUPs), dizziness and hypersensitivity.

6.1 Clinical Trials Experience

Because clinical trials are conducted under widely varying conditions, adverse reaction rates observed in the clinical trials of one drug cannot be directly compared to rates in clinical trials of another drug and may not reflect the rates observed in practice.

The safety, efficacy and pharmacokinetics of AFSTYLA have been evaluated in 258 previously treated patients (PTPs) and 24 previously untreated patients (PUPs) with severe hemophilia A (<1% endogenous Factor VIII activity) who received at least one dose of AFSTYLA as part of either routine prophylaxis, on-demand treatment of bleeding episodes or perioperative management in two completed clinical trials (an adult/adolescent study [≥12 to 65 years of age] and a pediatric study [<12 years of age]), and an extension study (0 to ≤65 years of age PTPs and 0 to ≤5 years old PUPs). Patients with a history of, or current FVIII inhibitors, or any first order family history of FVIII inhibitors, patients with known hypersensitivity (allergic reaction or anaphylaxis) to any FVIII product or hamster protein, and patients with evidence of thrombosis, including deep vein thrombosis, stroke, pulmonary embolism, myocardial infarction and arterial embolus within 3 months prior to Day 1 of the study were excluded from study participation.

One hundred eight (38.3%) subjects were children <12 years of age (59 [20.9%] 0 to <6 years and 49 [17.4%] ≥6 to <12 years), 14 (5.0%) were adolescents (≥12 to <18 years), and 160 (56.7%) were adults (≥18 to ≤65 years). In PTPs there have been a total of 28,418 exposure days (EDs), with at least 28,492 injections of AFSTYLA administered. In the completed studies, a total of 185 subjects achieved at least 50 EDs, of whom 60 subjects achieved ≥100 EDs. In PUPs there have been a total number of 5909 EDs, with 5914 injections, 21 subjects achieved ≥50 EDs.

Adverse reactions (ARs) (summarized in Table 3) were reported for 14 of 258 (5.4%) subjects in all studies. An adverse reaction of hypersensitivity resulted in the withdrawal of one subject. Among PTPs no subject developed neutralizing antibodies (inhibitors) to Factor VIII. No PTPs and PUPs developed antibodies to host cell proteins. No events of anaphylaxis or thrombosis were reported.

Table 3. Adverse Reactions Reported for AFSTYLA (N=258) [Adverse reactions reported in adult/adolescent and pediatric studies in previously treated patients]
MedDRA System Organ Class | Adverse Reactions | Number of Subjects n (%)
Immune system disorders | Hypersensitivity | 4 (1.6)
Nervous system disorders | Dizziness | 2 (0.8)
 | Paresthesia | 1 (0.4)
Skin and subcutaneous tissue disorders | Rash | 1 (0.4)
Skin and subcutaneous tissue disorders | Erythema | 1 (0.4)
 | Pruritus | 1 (0.4)
General disorders and administration site conditions | Pyrexia | 1 (0.4)
General disorders and administration site conditions | Injection-site pain | 1 (0.4)
 | Chills | 1 (0.4)
 | Feeling hot | 1 (0.4)

6.2 Immunogenicity

All subjects were monitored for inhibitory and binding antibodies to AFSTYLA, and binding antibodies to chinese hamster ovary (CHO) host cell proteins prior to the first infusion of AFSTYLA, at defined intervals during the studies and at the end of study visit.

Data from a completed clinical trial in previously untreated patients (PUPs) aged ≤5 years indicate that:

- 12 (50%; 95% CI: [29.1%, 70.9%]) of 24 treated subjects developed an inhibitor to Factor VIII.
- Of 22 subjects with at least 50 EDs or who developed inhibitor at any time, 6 (27.3%) developed high titer inhibitors (≥ 5BU) and 6 (27.3%) developed low titer inhibitors (<5BU).

The overall median EDs until initial inhibitor development was 10 EDs (range: 4 to 23). Of the 12 subjects who tested positive for inhibitors, 11 subjects have remained in the trial; 9 experienced successful eradication of the inhibitor. The median (range) EDs to inhibitor eradication was 37 (16 to 194). The median (range) time to inhibitor eradication was 14.3 (7.7 to 64.4) weeks. Two subjects with high titer inhibitors remain inhibitor positive: one subject was withdrawn from the immune tolerance induction (ITI) substudy after approximately 12 months, another subject completed ITI substudy after approximately 24 months.

No PTPs developed neutralizing antibodies (inhibitors) to Factor VIII or antibodies against CHO host cell proteins at any time during the completed clinical studies. Four subjects in the adult/adolescent study and 10 subjects in the pediatric study were negative for non-neutralizing anti-drug antibodies (ADAs) at screening and turned positive during the clinical study. Two of the adult/adolescent subjects and three of the pediatric subjects who developed ADAs were negative at end of study visit. No adverse events were associated with the development of ADAs. The detection of antibody formation is highly dependent on the sensitivity and specificity of the assay. Additionally, the observed incidence of antibody positivity in an assay may be influenced by several factors, including assay methodology, sample handling, timing of sample collection, concomitant medications, and underlying disease. For these reasons, it may be misleading to compare the incidence of antibodies to AFSTYLA with the incidence of antibodies to other products.

6.3 Postmarketing Experience

The following adverse reaction has been identified during post-approval use of AFSTYLA. Because these reactions are reported voluntarily from a population of uncertain size, it is not always possible to reliably estimate their frequency or establish a causal relationship to drug exposure.

Blood and lymphatic systems disorders: Factor VIII inhibitor development

8 USE IN SPECIFIC POPULATIONS

8.1 Pregnancy

Risk Summary

There are no data with AFSTYLA use in pregnant women to inform on drug-associated risk. No developmental or animal reproduction toxicity studies were conducted with AFSTYLA. Thus, the risk of developmental toxicity including, structural abnormalities, embryo-fetal and/or infant mortality, functional impairment, and alterations to growth is not known. In the US general population, the estimated background risk of major birth defects occurs in 2-4% of the general population and miscarriage occurs in 15-20% of clinically recognized pregnancies.

8.2 Lactation

Risk Summary

There is no information regarding the excretion of AFSTYLA in human milk, the effect on the breastfed infant, or the effects on milk production. The developmental and health benefits of breastfeeding should be considered along with the mother's clinical need for AFSTYLA and any potential adverse effects on the breastfed infant from AFSTYLA or from the underlying maternal condition.

8.4 Pediatric Use

Safety and efficacy studies with AFSTYLA have been performed in 98 PTPs <18 years of age and in 24 PUPs ≤5 years. Fourteen adolescent subjects ≥12 to <18 years were enrolled in the adult/adolescent safety and efficacy study. Thirty-five subjects 0 to <6 years and 49 subjects ≥6 to <12 years were enrolled in a pediatric safety and efficacy study [see Adverse Reactions (6.1), Clinical Pharmacology (12.3), and Clinical Studies (14)]. Because clearance (based on per kg body weight) has been shown to be higher in the pediatric population 0 to <12 years, more frequent or higher doses of AFSTYLA based on body weight may be needed [see Clinical Pharmacology (12.3)].

8.5 Geriatric Use

Clinical studies of AFSTYLA did not include subjects over 65 years to determine whether or not they respond differently from younger subjects.

11 DESCRIPTION

AFSTYLA is a single-chain recombinant Factor VIII produced in chinese hamster ovary (CHO) cells. It is a construct where the B-domain occurring in wild type full-length Factor VIII has been truncated and 4 amino acids of the adjacent acidic a3 domain were removed (amino acids 765 to 1652 of full-length Factor VIII). AFSTYLA is expressed as a single-chain Factor VIII molecule with covalent linkage between heavy and light chains; thereby keeping the molecule in the single-chain form resulting in increased stability and increased von Willebrand Factor (VWF) affinity. Except for a new N-glycosylation site at the junction between heavy and light chains, the post-translational modifications are comparable to endogenous Factor VIII.

AFSTYLA is purified by a controlled multi-step process including two virus reduction steps complementing each other in their mode of action. No human or animal derived proteins are used in the purification or formulation processes.

AFSTYLA is a preservative-free, sterile, non-pyrogenic, lyophilized powder to be reconstituted with sterile water for injection (sWFI) for intravenous injection. AFSTYLA is available in single-dose vials containing the labeled amount of Factor VIII activity, expressed in IU. Each vial contains nominally 250, 500, 1000, 1500, 2000, 2500, or 3000 IU of AFSTYLA. The actual potency is labeled on each AFSTYLA vial and carton. After reconstitution of the lyophilized powder, all dosage strengths yield an almost colorless to slightly opalescent solution. The concentrations of excipients based on the vial size, as well as the amount of sWFI for reconstitution are provided in Table 4 below.

Table 4. Nominal Composition after Reconstitution with sWFI
Ingredient | 250 IU vial | 500 IU vial | 1000 IU vial | 1500 IU vial | 2000 IU vial | 2500 IU vial | 3000 IU vial
rVIII-Single Chain | 100 IU/mL | 200 IU/mL | 400 IU/mL | 300 IU/mL | 400 IU/mL | 500 IU/mL | 600 IU/mL
L-Histidine | 3.1 mg/mL | 3.1 mg/mL | 3.1 mg/mL | 3.1 mg/mL | 3.1 mg/mL | 3.1 mg/mL | 3.1 mg/mL
Polysorbate 80 | 0.2 mg/mL | 0.2 mg/mL | 0.2 mg/mL | 0.2 mg/mL | 0.2 mg/mL | 0.2 mg/mL | 0.2 mg/mL
Calcium chloride | 0.4 mg/mL | 0.4 mg/mL | 0.4 mg/mL | 0.4 mg/mL | 0.4 mg/mL | 0.4 mg/mL | 0.4 mg/mL
Sodium chloride | 16.4 mg/mL | 16.4 mg/mL | 16.4 mg/mL | 16.4 mg/mL | 16.4 mg/mL | 16.4 mg/mL | 16.4 mg/mL
Sucrose | 6 mg/mL | 6 mg/mL | 6 mg/mL | 6 mg/mL | 6 mg/mL | 6 mg/mL | 6 mg/mL
Water for Injection | 2.5 mL | 2.5 mL | 2.5 mL | 5 mL | 5 mL | 5 mL | 5 mL

The number of units of Factor VIII administered is expressed in IU, which are related to the current WHO standard for Factor VIII products. One IU of Factor VIII activity in plasma is equivalent to that quantity of Factor VIII in 1 mL of normal plasma. Factor VIII activity in plasma is expressed either as a percentage (relative to normal human plasma) or in IU (relative to an International Standard for Factor VIII in plasma).

12 CLINICAL PHARMACOLOGY

12.1 Mechanism of Action

AFSTYLA is a recombinant protein that replaces the missing Coagulation Factor VIII needed for effective hemostasis. AFSTYLA is a single polypeptide chain with a truncated B-domain that allows for a covalent bridge to link the Factor VIII heavy and light chains. AFSTYLA has demonstrated a higher VWF affinity relative to full-length rFVIII.^1 VWF stabilizes Factor VIII and protects it from degradation. Activated AFSTYLA has an amino acid sequence identical to endogenous FVIIIa.

12.2 Pharmacodynamics

Hemophilia A is an X-linked hereditary disorder of blood coagulation due to decreased levels of Factor VIII and results in bleeding into joints, muscles or internal organs, either spontaneously or as result of accidental or surgical trauma. Replacement therapy increases the plasma levels of Factor VIII enabling a temporary correction of the factor deficiency and correction of the bleeding tendencies.

12.3 Pharmacokinetics

Subjects ≥12 years

The pharmacokinetics (PK) of AFSTYLA were evaluated in 91 (81 adults ≥18 years and 10 adolescents ≥12 to <18 years) previously treated subjects following an intravenous injection of a single dose of 50 IU/kg.

The PK parameters (Table 5) were based on plasma Factor VIII activity measured by the chromogenic assay after the first dose (initial PK assessment). The PK profile obtained 3 to 6 months after the initial PK assessment was comparable with the PK profile obtained after the first dose.

Table 5. Pharmacokinetic Parameters (Arithmetic Mean, Coefficient of Variation [CV%]) in Adults and Adolescents Following a Single Injection of 50 IU/kg of AFSTYLA - Chromogenic Assay
PK Parameters | ≥18 years (N=81) | ≥12 to <18 years (N=10)
IR (IU/dL)/(IU/kg) | 2.00 (20.8) | 1.69 (24.8)
Cmax (IU/dL) | 106 (18.1) | 89.7 (24.8)
AUC0-inf (IU*h/dL) | 1960 (33.1) | 1540 (36.5)
t1/2 (h) | 14.2 (26.0) | 14.3 (33.3)
MRT (h) | 20.4 (25.8) | 20.0 (32.2)
CL (mL/h/kg) | 2.90 (34.4) | 3.80 (46.9)
Vss (mL/kg) | 55.2 (20.8) | 68.5 (29.9)
IR = incremental recovery recorded at 30 minutes after injection; Cmax = observed maximum plasma concentration; AUC0-inf = area under the Factor VIII activity time curve extrapolated to infinity; t1/2 = half-life; MRT = mean residence time; CL = body weight adjusted clearance; Vss = body weight adjusted volume of distribution at steady-state.

Children <12 years

Pharmacokinetic parameters of AFSTYLA were evaluated in 39 previously treated children (0 to <12 years) in open-label, multicenter studies following a 50 IU/kg intravenous injection of AFSTYLA.

Table 6 summarizes the PK parameters calculated from the pediatric data. These parameters were estimated based on the plasma Factor VIII activity over time profile.

Table 6. Comparison of Pharmacokinetic Parameters in Children by Age Category (Arithmetic Mean, Coefficient of Variation [CV%]) Following a Single Injection of 50 IU/kg of AFSTYLA - Chromogenic Assay
PK Parameters | 0 to <6 years (N=20) | ≥6 to <12 years (N=19)
IR (IU/dL)/(IU/kg) | 1.60 (21.1) | 1.66 (19.7)
Cmax (IU/dL) | 80.2 (20.6) | 83.5 (19.5)
AUC0-inf (IU*h/dL) | 1080 (31.0) | 1170 (26.3)
t1/2 (h) | 10.4 (28.7) | 10.2 (19.4)
MRT (h) | 12.4 (25.0) | 12.3 (16.8)
CL (mL/h/kg) | 5.07 (29.6) | 4.63 (29.5)
Vss (mL/kg) | 71.0 (11.8) | 67.1 (22.3)
IR = incremental recovery recorded at 30 minutes after injection for subjects 12 to <18 years and at 60 minutes after injection for subjects 1 to <12 years; Cmax = observed maximum plasma concentration; AUC = area under the Factor VIII activity time curve extrapolated to infinity; t1/2 = half-life; MRT = mean residence time; CL = body weight adjusted clearance; Vss = body weight adjusted volume of distribution at steady-state.

13 NONCLINICAL TOXICOLOGY

13.1 Carcinogenesis, Mutagenesis, Impairment of Fertility

Long-term animal studies investigating the carcinogenic effects of AFSTYLA have not been conducted. In vitro and in vivo testing of AFSTYLA for mutagenicity or effects on fertility were not performed.

14 CLINICAL STUDIES

The safety and efficacy of AFSTYLA were evaluated in two studies in PTPs: an open-label, multicenter, crossover safety, efficacy and pharmacokinetic study in adults/adolescents as well as in an open-label pharmacokinetic, efficacy and safety study in children. The safety and efficacy of AFSTYLA was also evaluated in previously untreated patients (PUPs) in an open-label, multicenter pharmacokinetic, efficacy and safety study. These studies characterized the PK of AFSTYLA and determined hemostatic efficacy in the control of bleeding events, the prevention of bleeding events in prophylaxis and in the adult/adolescent study determined hemostatic efficacy during perioperative management of bleeding in subjects undergoing surgical procedures.

The adult/adolescent study enrolled a total of 175 previously treated male subjects with severe hemophilia A (<1% endogenous Factor VIII activity). Subjects ranged in age from 12 to 65 years, including 14 adolescent subjects (≥12 to <18 years). Of the 175 enrolled subjects, 174 received at least one dose of AFSTYLA and 173 (99%) were evaluable for efficacy. A total of 161 subjects (92.5%) completed the study. A total of 120 (69.0%) subjects were treated for at least 50 EDs and 52 (29.9%) of those subjects were treated for at least 100 EDs. Subjects received a total of 14,592 injections with a median of 67.0 (range 1 to 395) injections per subject.

The pediatric study enrolled 84 previously treated male subjects with severe hemophilia A (35 subjects 0 to <6 years and 49 subjects ≥6 to <12 years). Of the 84 enrolled subjects, all received at least one dose of AFSTYLA and 83 (99%) were evaluable for efficacy. A total of 65 (77.4%) subjects were treated for at least 50 EDs and 8 (9.5%) of those subjects were treated for at least 100 EDs. Subjects received a total of 5,313 injections with a median of 59 (range 4 to 145) injections per subject.

On-demand Treatment and Control of Bleeding Episodes

In the adult/adolescent study a total of 848 bleeding episodes were treated with AFSTYLA and 835 received an efficacy assessment by the investigator. The majority of the bleeding episodes occurred in joints. The median dose per injection used to treat a bleeding episode was 31.7 IU/kg (range 6 to 84 IU/kg). Of the 848 bleeding episodes, 686 (81%) were controlled with a single AFSTYLA injection and another 107 (13%) were controlled with 2 injections. Fifty-five (6%) of the 848 bleeding episodes required 3 or more injections. For 94% of bleeding episodes the hemostatic efficacy rating by the investigator was either excellent or good.

In the pediatric study a total of 347 bleeding episodes were treated with AFSTYLA all of which received an efficacy assessment by the investigator. The majority of the bleeding episodes occurred in joints. The median dose per injection used to treat a bleeding episode was 27.3 IU/kg (range 16 to 76 IU/kg). Of the 347 bleeding episodes, 298 (86%) were controlled with a single AFSTYLA injection and another 34 (10%) were controlled with 2 injections. Fifteen (4%) of the 347 bleeding episodes required 3 or more injections. For 96% of bleeding episodes the hemostatic efficacy rating by the investigator was either excellent or good.

Assessment of response to treatment of bleeds by the investigator was as follows:

Excellent: Pain relief and/or improvement in signs of bleeding (i.e., swelling, tenderness, and/or increased range of motion in the case of musculoskeletal hemorrhage) within approximately 8 hours after the first infusion

Good: Pain relief and/or improvement in signs of bleeding at approximately 8 hours after the first infusion, but requires two infusions for complete resolution

Moderate: Probable or slight beneficial effect within approximately 8 hours after the first infusion; requires more than two infusions for complete resolution

No response: No improvement at all or condition worsens (i.e., signs of bleeding) after the first infusion and additional hemostatic intervention is required with another FVIII product, cryoprecipitate, or plasma for complete resolution.

Efficacy in control of bleeding episodes in both studies is summarized in Table 7.

Table 7. Efficacy of AFSTYLA in Control of Bleeding
Bleeding Episodes Treated | Adult and Adolescent (≥12 to 65 years of age) (N=848) | Pediatric (0 to <12 years of age) (N=347)
Number of injections
1 injection, n (%) | 686 (81%) | 298 (85.9%)
2 injections, n (%) | 107 (13%) | 34 (9.8%)
3 injections, n (%) | 29 (3%) | 8 (2.3%)
>3 injections, n (%) | 26 (3%) | 7 (2.0%)
Efficacy evaluation by investigator | (N=835) | (N=347)
Excellent or Good, n (%) | 783 (94%) | 334 (96.3%)
Moderate, n (%) | 52 (6%) | 12 (3.5%)
No response, n (%) | 0 | 1 (0.3%)

Routine Prophylaxis

Adult and Adolescent Study

In the adult/adolescent and pediatric studies, subjects received prophylaxis in a regimen that was determined by the investigator, taking into account the subject's Factor VIII treatment regimen used prior to enrollment and the subject's bleeding phenotype.

In the adult/adolescent study, 54% of the 146 subjects on prophylaxis received AFSTYLA 3 times weekly; 32% of subjects received AFSTYLA 2 times weekly; 6% received AFSTYLA every other day, and 8% of subjects received other regimens.

The annualized bleeding rate (ABR) was comparable between subjects on a 3 times weekly regimen (median ABR of 1.53) and those on a 2 times weekly regimen (median ABR of 0.00). The annualized spontaneous bleeding rate (AsBR) was also comparable between subjects on a 3 times weekly regimen (median AsBR of 0.0) and those on a 2 times weekly regimen (median AsBR of 0.0). The number of subjects who needed dose adjustments was comparable between the two groups (34.2% [27 subjects] for 3 times weekly and 27.7% [13 subjects] for twice weekly).

The median prescribed dose for subjects on a 3 times weekly prophylaxis regimen was 30 IU/kg (12 to 50 IU/kg). The median prescribed dose for subjects on a 2 times weekly regimen was 35 IU/kg (17 to 50 IU/kg).

The ABR in prophylaxis (median of 1.14) was significantly lower (p <0.0001) than the ABR that was observed in subjects treated on-demand (median of 19.64). Sixty-three of 146 subjects (43%) experienced no bleeding episodes while on prophylaxis. There were no severe or life-threatening bleeds (e.g., intracranial hemorrhage) in subjects receiving prophylaxis.

Pediatric Study

In the pediatric study, 54% of the 80 subjects on prophylaxis received AFSTYLA 2 times a week; 30% of subjects received AFSTYLA 3 times a week; 4% received AFSTYLA every other day; and 12% of subjects received other regimens.

Twenty-one of 80 subjects (26%) experienced no bleeding episodes while on prophylaxis. There was one severe bleed (hip joint hemorrhage) in the pediatric study that was successfully treated.

For subjects on prophylaxis the overall ABR was 3.69, with a median ABR of 2.30 for subjects on a 3 times a week regimen and 4.37 for subjects on a 2 times a week regimen. The median AsBR (0.00) was identical between subjects on the 3 times a week and 2 times a week regimens.

The median prescribed dose for subjects on a 3 times a week regimen was 32 IU/kg (19 to 50 IU/kg) and for subjects on a 2 times a week regimen was 35 IU/kg (20 to 57 IU/kg).

The ABRs for prophylaxis and on-demand in both studies are summarized in Table 8.

Table 8. Summary of Annualized Bleeding Rate (ABR) by AFSTYLA Treatment Regimen
 | Phase I/III Adult/Adolescent Study |  | Phase III Pediatric Study
 | Prophylaxis (N=146) | On-demand (N=27) | Prophylaxis (N=80) | On-demand (N=3)
Overall ABR Median (IQR [IQR = interquartile range, 25th percentile to 75th percentile]) | 1.14 (0–4.2) | 19.64 (6.2–46.5) | 3.69 (0–7.2) | 78.56 (35.1–86.6)
Annualized Spontaneous Bleeding Rate (AsBR) Median (IQR) | 0 (0–2.4) | 11.73 (2.8–36.5) | 0 (0–2.2) | 31.76 (0–42.7)
Number of subjects with zero bleeding episodes | 63 (43.2%) | 1 (3.7%) | 21 (26.3%) | 0

Perioperative Management of Bleeding

Thirteen subjects in the adult/adolescent study underwent a total of 16 surgical procedures. Overall, investigators assessed hemostatic efficacy of AFSTYLA in perioperative management of bleeding as excellent in 15 of 16 surgeries and as good in 1 of 16 surgeries (see Table 9). Median factor consumption pre- and intra-operatively was 89.4 IU/kg (range 40.5 to 108.6 IU/kg).

Assessment of hemostasis during surgical procedures by the investigator was as follows:

Excellent: Hemostasis clinically not significantly different from normal (e.g., achieved hemostasis comparable to that expected during similar surgery in a non-factor deficient patient) in the absence of other hemostatic intervention and estimated blood loss during surgery is not more than 20% higher than the predicted blood loss for the intended surgery

Good: Normal or mildly abnormal hemostasis in terms of quantity and/or quality (e.g., slight oozing, prolonged time to hemostasis with somewhat increased bleeding compared to a non-factor deficient patient in the absence of other hemostatic intervention) or estimated blood loss is >20%, but ≤30% higher than the predicted blood loss for intended surgery

Moderate: Moderately abnormal hemostasis in terms of quantity and/or quality (e.g., moderate hemorrhage that is difficult to control) with estimated blood loss greater than what is defined as good

Poor/No Response: Severely abnormal hemostasis in terms of quantity and/or quality (e.g., severe hemorrhage that is difficult to control) and/or additional hemostatic intervention required with another FVIII product, cryoprecipitate, or plasma for complete resolution.

Table 9. Efficacy of AFSTYLA in Perioperative Management of Bleeding
Procedure | Efficacy Evaluation | Factor Consumption (IU/kg) (pre- and intra-operatively)
Extraction of wisdom teeth | Excellent | 51.09
Abdominal hernia repair | Excellent | 47.89
Elbow replacement | Excellent | 108.58
Ankle arthroplasty | Excellent | 76.83
Knee replacement (5) | Excellent (4), Good (1) | 92.49 100.9 67.26 105.79 86.09
Cholecystectomy and Lengthening of the Achilles tendon combined with: Straightening of the right toes | Excellent Excellent | 105.95
Circumcision (3) | Excellent (3) | 99.04 92.74 81.5
Open reduction internal fixation (ORIF) right ankle | Excellent | 89.36
Hardware removal, Right ankle | Excellent | 40.45

15 REFERENCES

1. Zollner S, Raquet E, Claar Ph, Müller-Cohrs J, Metzner HJ, Weimer Th, Pragst I, Dickneite G, Schulte S. Non-clinical pharmacokinetics and pharmacodynamics of rVIII-SingleChain, a novel recombinant single-chain factor VIII, Thrombosis Research 2014; 134: 125-131.

16 HOW SUPPLIED/STORAGE AND HANDLING

AFSTYLA is supplied in a kit containing a lyophilized powder in a single-dose vial labeled with the amount of Factor VIII activity, expressed in international units (IU). Actual Factor VIII activity in International Units (IU) is stated on the AFSTYLA carton and vial label.

AFSTYLA is packaged with Sterile Water for Injection, USP (2.5 mL for reconstitution of 250, 500 or 1000 IU or 5 mL for reconstitution of 1500, 2000, 2500, or 3000 IU AFSTYLA), one Mix2Vial filter transfer set, and one sterile alcohol swab. Components are not made of natural rubber latex.

Table 10. How Supplied
Nominal Strength | Fill Size Color Indicator | Kit NDC
250 IU | Orange | 69911-474-02
500 IU | Blue | 69911-475-02
1000 IU | Green | 69911-476-02
1500 IU | Turquoise | 69911-480-02
2000 IU | Purple | 69911-477-02
2500 IU | Cool Grey | 69911-481-02
3000 IU | Yellow | 69911-478-02

Storage and Handling

- Store AFSTYLA in the original package to protect the AFSTYLA vials from light.
- Store AFSTYLA in powder form at 2°C to 8°C (36°F to 46°F). Do not freeze to avoid damage to the diluent vial. AFSTYLA can be stored at room temperature, not to exceed 25°C (77°F), for a single period of up to 3 months, within the expiration date printed on the carton and vial labels.
- Record the starting date of room temperature on the unopened product carton. Once stored at room temperature, do not return the product to the refrigerator. The shelf-life then expires after storage at room temperature for 3 months, or after the expiration date on the product vial, whichever is earlier.
- Do not use AFSTYLA after the expiration date indicated on the vial.
- The reconstituted product (after mixing dry product with diluent) can be stored at 2°C to 8°C (36°F to 46°F), or at room temperature, not to exceed 25°C (77°F), for up to 4 hours.
- Protect from direct sunlight.
- After reconstitution, if the product is not used within 4 hours, it must be discarded.
- Do not use AFSTYLA if the reconstituted solution is cloudy or has particulate matter.
- Discard any unused AFSTYLA.

17 PATIENT COUNSELING INFORMATION

Advise patients to:

- Read the FDA-approved Patient Labeling (Patient Product Information and Instructions for Use).
- Discontinue use of AFSTYLA in case of a hypersensitivity reaction and contact their healthcare provider and/or seek emergency care, depending on the severity of the reaction. Early signs of hypersensitivity reactions may include hives, itching, facial swelling, tightness of the chest, and wheezing [see Warnings and Precautions (5.1)].
- Contact their healthcare provider or hemophilia treatment facility for further treatment and/or assessment if they experience a lack of a clinical response to Factor VIII replacement therapy, as in some cases this may be a manifestation of an inhibitor [see Warnings and Precautions (5.2)].
- Report any adverse reactions or problems following AFSTYLA administration to their healthcare provider.

Manufactured by:
CSL Behring GmbH
35041 Marburg, Germany

for:
CSL Behring Lengnau AG
Biotech Innovation Park
2543 Lengnau, Switzerland
US License No. 2009

Distributed by:
CSL Behring LLC
Kankakee, IL 60901 USA

Mix2Vial® is a registered trademark of West Pharma. Services IL, Ltd., a subsidiary of West Pharmaceuticals Services, Inc.

For Patent information: www.cslbehring.com/products/patents

FDA-Approved Patient Labeling – Patient Product Information (PPI)

AFSTYLA / af sty̆ ̍lah /

Antihemophilic Factor (Recombinant), Single Chain

Freeze-Dried Powder for Reconstitution

This leaflet summarizes important information about AFSTYLA. Please read it carefully before using AFSTYLA. This information does not take the place of talking with your healthcare provider, and it does not include all of the important information about AFSTYLA. If you have any questions after reading this, ask your healthcare provider.

What is the most important information I need to know about AFSTYLA?

- Your healthcare provider or hemophilia treatment center will instruct you on how to do an infusion on your own.
- Carefully follow your healthcare provider's instructions regarding the dose and schedule for infusing this medicine.

What is AFSTYLA?

- AFSTYLA, Antihemophilic Factor (Recombinant), Single Chain is a medicine used to replace clotting Factor VIII that is missing in patients with hemophilia A.
- Hemophilia A is an inherited bleeding disorder that prevents blood from clotting normally.
- Does not contain human plasma-derived proteins or albumin.
- Your healthcare provider may give you this medicine when you have surgery.
- Is used to treat and control bleeding in all patients with hemophilia A.
- Can reduce the number of bleeding episodes when used regularly (prophylaxis) and reduce the risk of joint damage due to bleeding.
- Is not used to treat von Willebrand disease.

Who should not use AFSTYLA?

You should not use AFSTYLA if you:

- Have had a life-threatening allergic reaction to it in the past.
- Are allergic to its ingredients or hamster proteins.

Tell your healthcare provider if you are pregnant or breastfeeding because AFSTYLA may not be right for you.

What should I tell my healthcare provider before using AFSTYLA?

Tell your healthcare provider if you:

- Have or have had any medical problems.
- Take any medicines, including prescription and non-prescription medicines, such as over-the-counter medicines, supplements or herbal remedies.
- Have any allergies, including allergies to hamster proteins.
- Are pregnant or planning to become pregnant. It is not known if AFSTYLA may harm your unborn baby.
- Are breastfeeding. It is not known if AFSTYLA passes into the milk or if it can harm your baby.
- Have been told you have inhibitors to Factor VIII (because this medicine may not work for you).

How should I use AFSTYLA?

- Administer directly into the bloodstream.
- Use as ordered by your healthcare provider.
- You should be trained on how to do intravenous injections by your healthcare provider or hemophilia treatment center. Once trained, many patients with hemophilia A are able to inject this medicine by themselves or with the help of a family member.
- Your healthcare provider will tell you how much to use based on your weight, the severity of your hemophilia A, and where you are bleeding.
- You may need to have blood tests done after getting AFSTYLA to be sure that your blood level of Factor VIII is high enough to clot your blood.
- Call your healthcare provider right away if your bleeding does not stop after taking this medicine.

What are the possible side effects of AFSTYLA?

- Allergic reactions may occur. Immediately stop treatment and call your healthcare provider right away if you get a rash or hives, itching, tightness of the chest or throat, difficulty breathing, light-headedness, dizziness, nausea, or decrease in blood pressure.
- Your body may form inhibitors to Factor VIII. An inhibitor is a part of the body's defense system. If you form inhibitors, it may stop this medicine from working properly. The greatest risk of this occurring is in previously untreated patients. Your healthcare provider may need to test your blood for inhibitors from time to time.
- Common side effects are dizziness and allergic reactions.
- These are not the only side effects possible. Tell your healthcare provider about any side effect that bothers you or does not go away.

What are the AFSTYLA dosage strengths?

AFSTYLA comes in seven different dosage strengths: 250, 500, 1000, 1500, 2000, 2500, or 3000 International Units (IU) as provided in Table 1. The actual strength is printed on the carton and vial label.

Table 1. AFSTYLA Dosage Strengths
Fill Size Color Indicator | Strengths
Orange | Dosage strength of approximately 250 IU per vial
Blue | Dosage strength of approximately 500 IU per vial
Green | Dosage strength of approximately 1000 IU per vial
Turquoise | Dosage strength of approximately 1500 IU per vial
Purple | Dosage strength of approximately 2000 IU per vial
Cool Grey | Dosage strength of approximately 2500 IU per vial
Yellow | Dosage strength of approximately 3000 IU per vial

Always check the actual dosage strength printed on the label to make sure you are using the strength prescribed by your healthcare provider.

How should I store AFSTYLA?

- Store this medicine in the original package to protect the vials from light.
- Store this medicine in powder form at 2°C to 8°C (36°F to 46°F). Do not freeze to avoid damage to the diluent vial. It can be stored at room temperature, not to exceed 25°C (77°F), for a single period of up to 3 months, within the expiration date printed on the carton and vial labels.
- If stored at room temperature, record the date that this medicine is removed from refrigeration on the top flap of the carton in the area provided. After storage at room temperature, do not return the product to the refrigerator. The powder form for the product then expires after storage at room temperature for 3 months, or after the expiration date on the product vial, whichever is earlier.
- The reconstituted product (after mixing dry product with diluent) can be stored for 4 hours at a temperature not to exceed 25°C (77°F). Protect from direct sunlight. After reconstitution, if the product is not used within 4 hours, it must be discarded.

What else should I know about AFSTYLA?

- Medicines are sometimes prescribed for purposes other than those listed here. Do not use this medicine for a condition for which it is not prescribed. Do not share with other people, even if they have the same symptoms that you have.

Instructions for Use of AFSTYLA

For intravenous use after reconstitution only

This medicine is infused into a vein. Your healthcare provider or hemophilia treatment center should teach you how to do infusions on your own.

Always follow the specific instructions given by your healthcare provider. The steps listed below are general guidelines for using AFSTYLA. If you are unsure of the instructions, call your healthcare provider before using AFSTYLA. Call your healthcare provider right away if bleeding is not controlled after using AFSTYLA. Your healthcare provider will prescribe the dose that you should take. You may need to take blood tests from time to time. Talk to your healthcare provider before traveling. Dispose of all unused solution, empty vial(s), and other used medical supplies in an appropriate medical waste container.

- Always work on a clean flat surface and wash your hands before performing the reconstitution procedures.
- Use only the components for reconstitution that are provided with each package.
- If a package is opened or damaged, do not use and contact your healthcare provider.
- Do not use AFSTYLA beyond the expiration date on the vial and carton labels. If stored at room temperature, the dry product (prior to reconstitution) expires after storage at room temperature for 3 months or after the expiration date on the product vial, whichever is earlier.
- Look at the mixed (reconstituted) solution. Do not use AFSTYLA if the reconstituted solution is cloudy, contains any particles, or is discolored.
- AFSTYLA is for single-dose only and contains no preservatives. Discard partially used vials.

AFSTYLA Reconstitution Instructions

1. Ensure that the AFSTYLA vial and diluent vial are at room temperature.
2. Place the AFSTYLA vial, diluent vial, and Mix2Vial® transfer set on a flat surface.
3. Remove AFSTYLA and diluent vial flip caps. Wipe the stoppers with the sterile alcohol swab provided and allow the stoppers to dry prior to opening the Mix2Vial transfer set package.
4. Open the Mix2Vial transfer set package by peeling away the lid (Fig. 1). Leave the Mix2Vial transfer set in the clear package.
  Fig. 1
5. Place the diluent vial on a flat surface and hold the vial tightly. Grip the Mix2Vial transfer set together with the clear package and push the plastic spike at the blue end of the Mix2Vial transfer set firmly through the center of the stopper of the diluent vial (Fig. 2).
  Fig. 2
6. Carefully remove the clear package from the Mix2Vial transfer set. Make sure that you pull up only the clear package, not the Mix2Vial transfer set (Fig. 3).
  Fig. 3
7. With the AFSTYLA vial placed firmly on a flat surface, invert the diluent vial with the Mix2Vial transfer set attached and push the plastic spike of the transparent adapter firmly through the center of the stopper of the AFSTYLA vial (Fig. 4). The diluent will automatically transfer into the AFSTYLA vial.
  Fig. 4
8. With the diluent and AFSTYLA vial still attached to the Mix2Vial transfer set, gently swirl the AFSTYLA vial to ensure that the AFSTYLA is fully dissolved (Fig. 5). Do not shake the vial.
  Fig. 5
9. With one hand, grasp the AFSTYLA side of the Mix2Vial transfer set and with the other hand grasp the blue diluent-side of the Mix2Vial transfer set, and unscrew the set into two pieces. (Fig. 6).
  Fig. 6
10. Draw air into an empty, sterile syringe. While the AFSTYLA vial is upright, screw the syringe to the Mix2Vial transfer set. Inject air into the AFSTYLA vial. While keeping the syringe plunger pressed, invert the system upside down and draw the concentrate into the syringe by pulling the plunger back slowly. (Fig. 7).
  Fig. 7
11. Now that the concentrate has been transferred into the syringe, firmly grasp the barrel of the syringe (keeping the plunger facing down) and unscrew the syringe from the Mix2Vial transfer set (Fig. 8).
  Fig. 8
12. After reconstitution, infuse immediately or within 4 hours. The mixed (reconstituted) solution may be stored at room temperature, not to exceed 25°C (77°F), for up to 4 hours. Do not freeze. Protect from direct sunlight.
13. Record treatment – Remove the peel-off portion of the label from each vial used, and affix it to the patient's treatment diary/log book or scan the vial if recording the infusion electronically.
14. If the dose requires more than one vial, use a separate unused Mix2Vial transfer set for each product vial. Repeat step 10 to pool the contents into one syringe.

Administration (intravenous injection)

- Do not mix AFSTYLA in the same tubing or container with other medicinal products.
- Attach the syringe containing the mixed (reconstituted) solution to a sterile infusion set and give an injection as directed by your healthcare provider or hemophilia treatment center.
- Administer intravenously. Do not exceed infusion rate of 10 mL per minute.

Resources at CSL Behring available to the patient:
For Adverse Reaction Reporting contact:
CSL Behring Pharmacovigilance Department at 1-866-915-6958

Contact CSL Behring to receive more product information:
Patient Support Hotline at 1-800-676-4266

For more information, visit www.AFSTYLA.com

Manufactured by:
CSL Behring GmbH
35041 Marburg, Germany

for:
CSL Behring Lengnau AG
Biotech Innovation Park
2543 Lengnau, Switzerland
US License No. 2009

Distributed by:
CSL Behring LLC
Kankakee, IL 60901 USA

Mix2Vial® is a registered trademark of West Pharma. Services IL, Ltd., a subsidiary of West Pharmaceuticals Services, Inc.

Revised: 6/2023

PRINCIPAL DISPLAY PANEL - Kit Carton - 250 IU

NDC 69911-474-02

250 IU Range

AFSTYLA®
Antihemophilic Factor (Recombinant),
Single Chain

One single-dose vial containing lyophilized powder for reconstitution.

For Intravenous Administration Only

CSL Behring

PRINCIPAL DISPLAY PANEL - Kit Carton - 500 IU

NDC 69911-475-02

500 IU Range

AFSTYLA®

Antihemophilic Factor (Recombinant),
Single Chain

One single-dose vial containing lyophilized powder for reconstitution.

For Intravenous Administration Only

CSL Behring

PRINCIPAL DISPLAY PANEL - Kit Carton - 1000 IU

NDC 69911-476-02

1000 IU Range

AFSTYLA®
Antihemophilic Factor (Recombinant),
Single Chain

One single-dose vial containing lyophilized powder for reconstitution.

For Intravenous Administration Only

CSL Behring

PRINCIPAL DISPLAY PANEL - Kit Carton - 2000 IU

NDC 69911-477-02

2000 IU Range

AFSTYLA®
Antihemophilic Factor (Recombinant),
Single Chain

One single-dose vial containing lyophilized powder for reconstitution.

For Intravenous Administration Only

CSL Behring

PRINCIPAL DISPLAY PANEL - Kit Carton - 3000 IU

NDC 69911-478-02

3000 IU Range

AFSTYLA®
Antihemophilic Factor (Recombinant),
Single Chain

One single-dose vial containing lyophilized powder for reconstitution.

For Intravenous Administration Only

CSL Behring

PRINCIPAL DISPLAY PANEL - Kit Carton - 1500 IU

NDC 69911-480-02

1500 IU Range

AFSTYLA®

Antihemophilic Factor (Recombinant),
Single Chain

One single-dose vial containing lyophilized powder for reconstitution.

For Intravenous Administration Only

CSL Behring

PRINCIPAL DISPLAY PANEL - Kit Carton - 2500 IU

NDC 69911-481-02

2500 IU Range

AFSTYLA®
Antihemophilic Factor (Recombinant),
Single Chain

One single-dose vial containing lyophilized powder for reconstitution.

For Intravenous Administration Only

CSL Behring